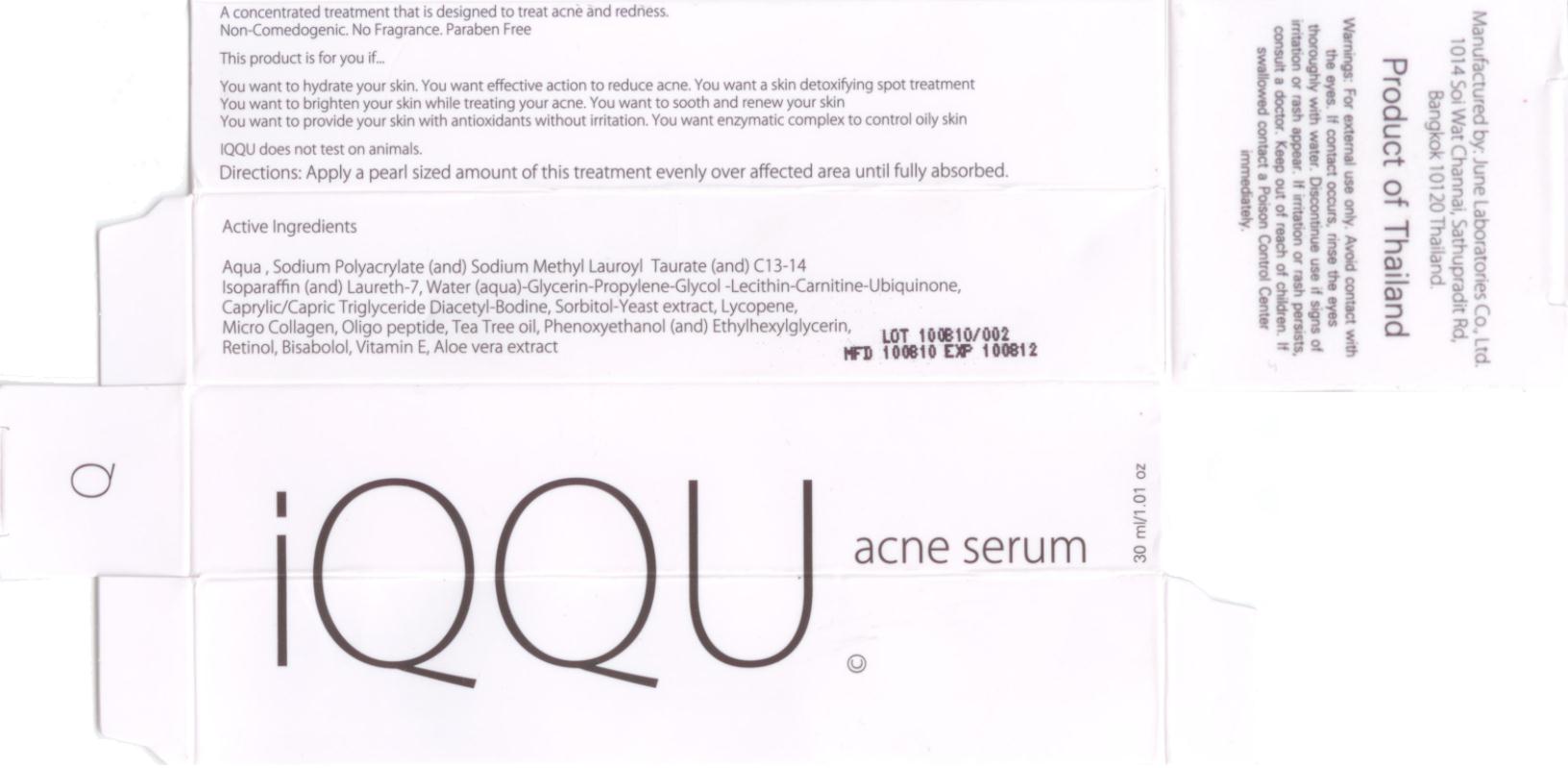 DRUG LABEL: IQQU Acne Serum
NDC: 50403-226 | Form: LOTION
Manufacturer: IQQU USA Co.
Category: otc | Type: HUMAN OTC DRUG LABEL
Date: 20101024

ACTIVE INGREDIENTS: CARNITINE 0.012 g/1 g; UBIDECARENONE 0.0012 g/1 g; LECITHIN, SOYBEAN 0.024 g/30 g
INACTIVE INGREDIENTS: TEA TREE OIL; RETINOL; ALOE VERA LEAF; WATER; MEDIUM-CHAIN TRIGLYCERIDES; SORBITOL; LYCOPENE; PHENOXYETHANOL; LEVOMENOL; ALPHA-TOCOPHEROL; LAURETH-7; C13-14 ISOPARAFFIN; PROPYLENE GLYCOL; GLYCERIN

Acne Serum

IQQU
Acne Serum

Active Ingredient

Water (aqua) Lecithin-Carnitine-Ubiquione

Purpose

A concentraged treatment that is designed to treat acne and redness.

Directions

Apply a pearl sized amount of treatment evenly over affected area until fully absorbed.

Warnings

For external use only. Avoid contact with the eyes. If contact occurs, rinse the eyes thoroughly with water. Discontinue use if sign of irritation or rash appear. If irritation or rash persists, consult a doctor.

This product is for you if

You want to hydrate your skin, You want effective action to reduce acne. You want a skin detoxifying spot treatment.
You want to brighten your skin while treating your acne. You want to smooth and renew your skin.
You want to provide your skin with antioxidants without irritation. You want enzymatic complex to control oily skin.

IQQU does not test on animals.

Keep out of reach of children.

If swallowed contact a Poison Control Center immediately.

Inactive Ingredients

Caprylic/Capric Triglyceride, Diacetyl-Bodine, Sorbitol-Yeast extract, Lycopene, Micro Collagen, Oligo peptide, Tea Tree oil, Phenoxyethanol (and) Ethylhexyglycerin, Retinol, Bisabolol, Vitamin E, Aloe vera extract, Aqua, Sodium Polyacrylate (and) Sodium Methyl Lauroyl Taurate (and) C13-14 Isoparaffin (and) Laureth-7, Glycerin, Propylene-Glycol

Manufactured by: June Laboratories Co., Ltd.

1014 Soi Wat Channai, Sathupradit Rd,

Bangkok 10120 Thailand.

Product of Thailand

www.iqqubeauty.com

PRINCIPAL DISPLAY PANEL

Package Label – 30 mL

IQQU Acne Serum

30 mL /1.01 oz